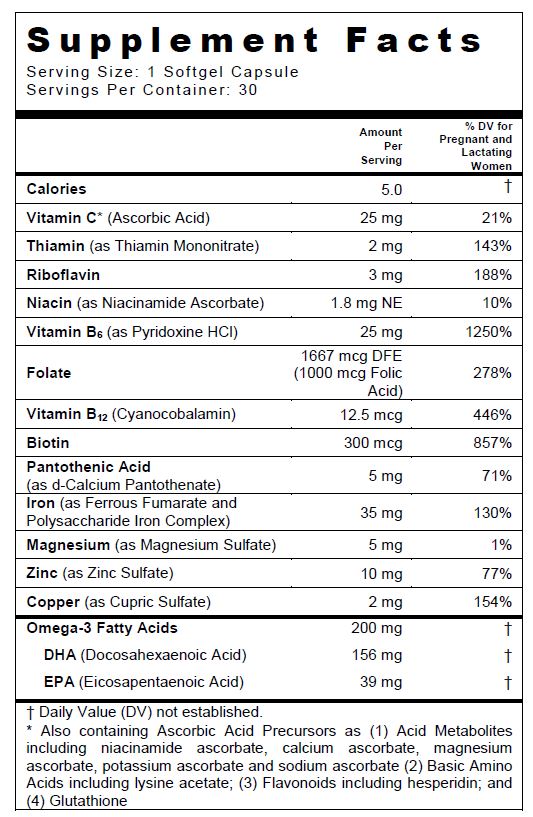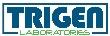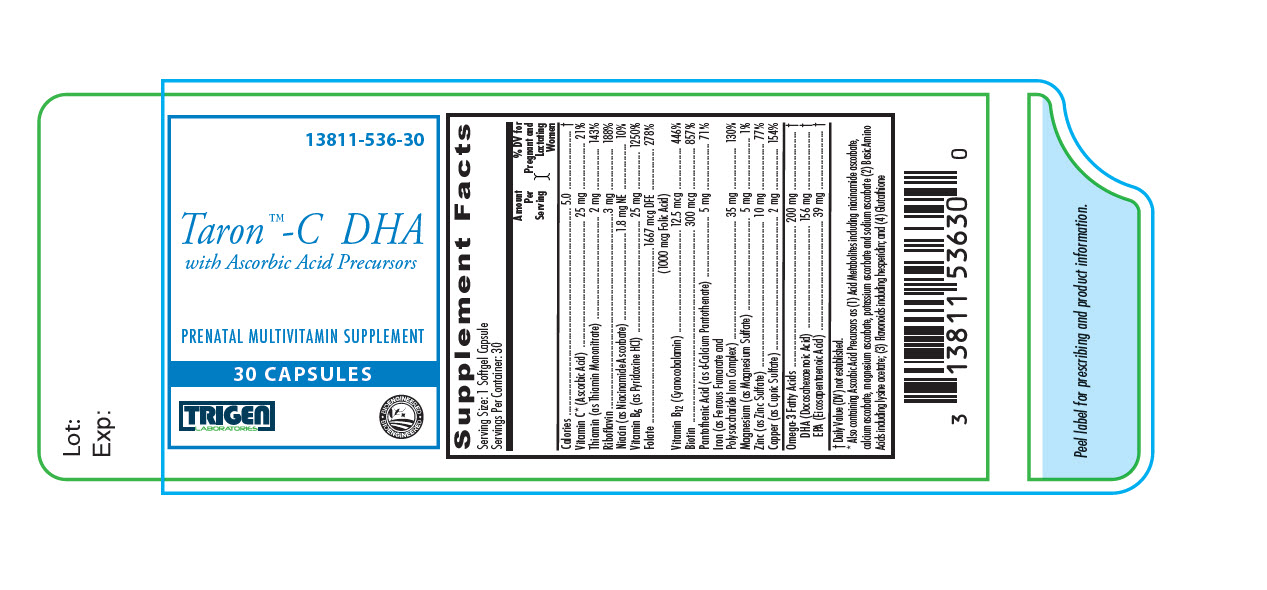 DRUG LABEL: Taron-C DHA
NDC: 13811-536 | Form: CAPSULE
Manufacturer: Trigen Laboratories, LLC
Category: other | Type: DIETARY SUPPLEMENT
Date: 20211222

ACTIVE INGREDIENTS: ferrous fumarate 17.5 mg/1 1; IRON 17.5 mg/1 1; ascorbic acid 25 mg/1 1; folic acid 1 mg/1 1; thiamine mononitrate 2 mg/1 1; riboflavin 3 mg/1 1; Niacin 1.8 mg/1 1; calcium pantothenate 5 mg/1 1; pyridoxine Hydrochloride 25 mg/1 1; biotin 300 ug/1 1; cyanocobalamin 12.5 ug/1 1; Cupric Sulfate 2 mg/1 1; MAGNESIUM SULFATE ANHYDROUS 5 mg/1 1; zinc sulfate 10 mg/1 1; Omega-3 fatty acids 200 mg/1 1
INACTIVE INGREDIENTS: GELATIN TYPE B BOVINE (160 BLOOM); glycerin; water; lecithin, soybean; yellow wax; titanium dioxide; ethyl vanillin; FD&C blue No. 1; SORBITOL; ORANGE OIL

Taron™-C DHA
with Ascorbic Acid Precursors

SUPPLEMENT FACTS

Other Ingredients: Bovine Gelatin, Glycerin, Yellow Beeswax, Soy Lecithin, Purified Water, Orange Cream Flavor O.S, Sorbitol, Titanium Dioxide, Ethyl Vanillin, FD&C Blue #1.

THIS PRODUCT CONTAINS SOY AND FISH (TUNA, MAY INCLUDE ANCHOVY AND/OR SARDINE).

Taron™-C DHA is a prescription multivitamin/mineral indicated to provide omega-3 fatty acid supplementation throughout pregnancy, during the postnatal period for both lactating and non-lactating mothers, and throughout the childbearing years. Taron™-C DHA may be useful in improving the nutritional status of women prior to conception.

CONTRAINDICATIONS

Taron™-C DHA is contraindicated in patients with a known hypersensitivity to any of the ingredients including soy or fish products. All iron compounds are contraindicated in patients with hemochromatosis, hemosiderosis, or hemolytic anemias.

WARNINGS

Administration of omega-3 fatty acids should be avoided in patients taking anticoagulants and in those known to have an inherited or acquired predisposition to bleeding.

WARNING: Accidental overdose of iron-containing products is a leading cause of fatal poisoning in children under 6. KEEP THIS PRODUCT OUT OF REACH OF CHILDREN. In case of accidental overdose, call a doctor or poison control center immediately.

PRECAUTIONS

Folic acid alone is an improper therapy in the treatment of pernicious anemia and other megaloblastic anemias where vitamin B12 is deficient. Folic acid in doses above 0.1 mg daily may obscure pernicious anemia in that hematologic remission can occur while neurologic manifestations remain progressive.

The patient’s medical conditions and consumption of other drugs, herbs, and/or supplements should be considered.

Pediatric Use: Safety and effectiveness in pediatric populations have not been established.

Geriatric Use: Safety and effectiveness in elderly populations have not been established.

Biotin levels higher than the recommended daily allowance may cause interference with some laboratory tests, including cardiovascular diagnostic tests (e.g. troponin) and hormone tests, and may lead to incorrect test results. Tell your healthcare provider about all prescription and over-the-counter medicines, vitamins, and dietary supplements that you take, including biotin.

DRUG INTERACTIONS

Taron™-C DHA is not recommended for and should not be given to patients receiving levodopa because the action of levodopa is antagonized by pyridoxine. There is a possibility of increased bleeding due to pyridoxine interaction with anticoagulants (e.g., Aspirin, Heparin, Clopidogrel).

ADVERSE REACTIONS

Folic Acid: Allergic sensitization has been reported following both oral and parenteral administration of folic acid.

Ferrous Fumarate: Gastrointestinal disturbances (anorexia, nausea, diarrhea, constipation) occur occasionally, but are usually mild and may subside with continuation of therapy. Although the absorption of iron is best when taken between meals, giving Taron™-C DHA after meals may control occasional G.I. disturbances. Taron™-C DHA is best absorbed when taken at bedtime.

OVERDOSAGE

Iron is toxic. Acute overdosage of iron may cause nausea and vomiting and, in severe cases, cardiovascular collapse and death. Other symptoms include pallor and cyanosis, melena, shock, drowsiness, and coma. The estimated overdose of orally ingested iron is 300-mg/kg body weight. When overdoses are ingested by children, severe reactions, including fatalities, have resulted. Taron™-C DHA should be stored beyond the reach of children to prevent against accidental iron poisoning.

Treatment: For specific therapy, exchange transfusion and chelating agents should be used. For general management, perform gastric lavage with sodium bicarbonate solution or milk. Administer intravenous fluids and electrolytes and use oxygen.

DESCRIPTION

Taron™-C DHA is a blue, oval softgel capsule containing a dark brown oil, imprinted with “T536”.

DIRECTIONS FOR USE

Adults (over 12 years of age) may take one capsule daily between meals or as prescribed by a physician. Do not exceed recommended dosage. Do not administer to children under the age of 12.

HOW SUPPLIED

Taron™-C DHA is dispensed in child-resistant bottles of 30 softgel capsules.

PRODUCT CODE 13811-536-30

STORAGE

Store at 20°-25°C (68°-77°F); excursions permitted to 15°-30°C (59°- 86°F). [See USP Controlled Room Temperature].

KEEP OUT OF REACH OF CHILDREN

For use on the order of a healthcare practitioner.

Call your doctor about side effects. To report side effects, call Trigen Laboratories, LLC at 1-770-509-4500 or FDA at 1-800-FDA-1088 or www.fda.gov/medwatch.

Rev. 12/2021
PLR-TARONCDHA-00001-2

Manufactured for:
Trigen Laboratories, LLC
Alpharetta, GA 30005
www.trigenlab.com

PRINCIPAL DISPLAY PANEL - 30 Capsule Bottle Label

13811-536-30

Taron™-C DHA
with Ascorbic Acid Precursors

PRENATAL MULTIVITAMIN SUPPLEMENT

30 CAPSULES

TRIGEN
LABORATORIES